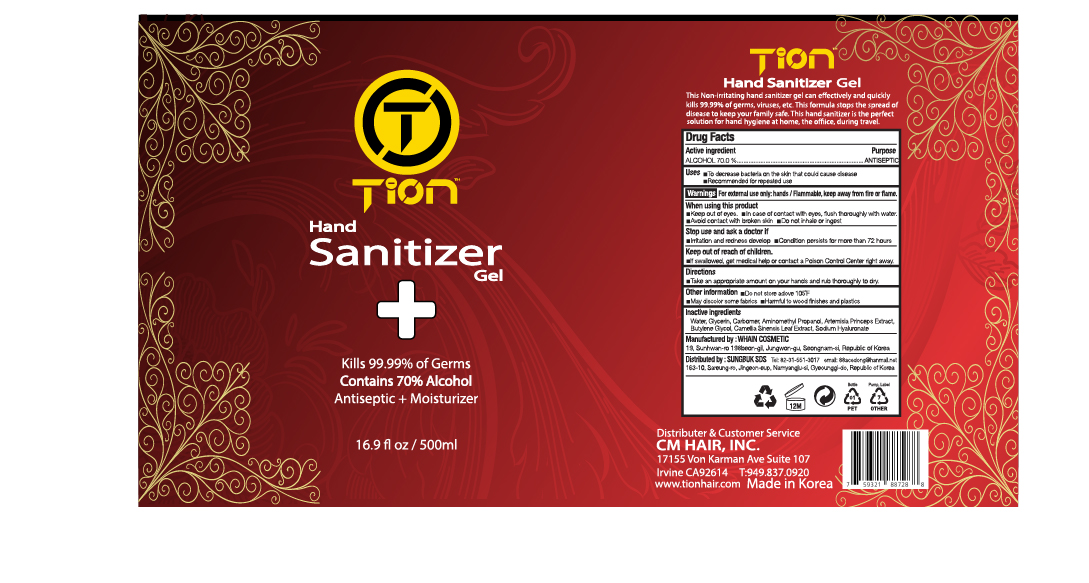 DRUG LABEL: Tion Hand Sanitizer Gel
NDC: 73823-750 | Form: GEL
Manufacturer: WHAIN COSMETIC
Category: otc | Type: HUMAN OTC DRUG LABEL
Date: 20200512

ACTIVE INGREDIENTS: ALCOHOL 350 mL/500 mL
INACTIVE INGREDIENTS: AMINOMETHYL PROPANEDIOL; GLYCERIN; HYALURONATE SODIUM; BUTYLENE GLYCOL; CARBOMER HOMOPOLYMER, UNSPECIFIED TYPE; WATER; ARTEMISIA PRINCEPS LEAF; GREEN TEA LEAF

Tion Hand Sanitizer Gel 500 ml : 73823-750-01